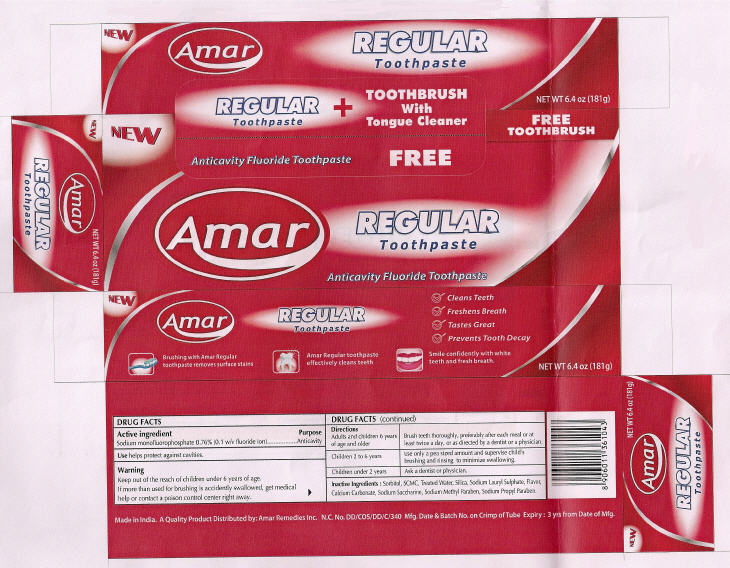 DRUG LABEL: Amar 
NDC: 41499-106 | Form: PASTE, DENTIFRICE
Manufacturer: Amar Remedies Limited - Mumbai
Category: otc | Type: HUMAN OTC DRUG LABEL
Date: 20091222

ACTIVE INGREDIENTS: Sodium monofluorophosphate 0.76 g/100 g
INACTIVE INGREDIENTS: Water; Silicon Dioxide

Amar
REGULAR
Fluoride Toothpaste

DRUG FACTS

Active ingredient

Sodium monofluorophosphate 0.76% (0.1 w/v fluoride ion)

Purpose

Anticavity

Use

helps protect against cavities.

Warning

KEEP OUT OF REACH OF CHILDREN

Keep out of the reach of children under 6 years of age.

If more than used for brushing is accidently swallowed, get medical help or contact a poison control center right away.

Directions

Adults and children 6 years of age and older | Brush teeth thoroughly, preferably after each meal or at least twice a day, or as directed by a dentist or a physician.
Children 2 to 6 years | Use only a pea sized amount and supervise child's brushing and rinsing to minimize swallowing.
Children under 2 years | Ask a dentist or physician.

Inactive Ingredients

Sorbitol, SCMC, Treated Water, Silica, Sodium Lauryl Sulphate, Flavor, Calcium Carbonate, Sodium Saccharine, Sodium Methyl Paraben, Sodium Propyl Paraben.

Distributed by: Amar Remedies Inc.

PRINCIPAL DISPLAY PANEL - 181 g Carton

NEW

Anticavity Fluoride Toothpaste

Amar

FREE TOOTHBRUSH

REGULAR
Toothpaste

Anticavity Fluoride Toothpaste